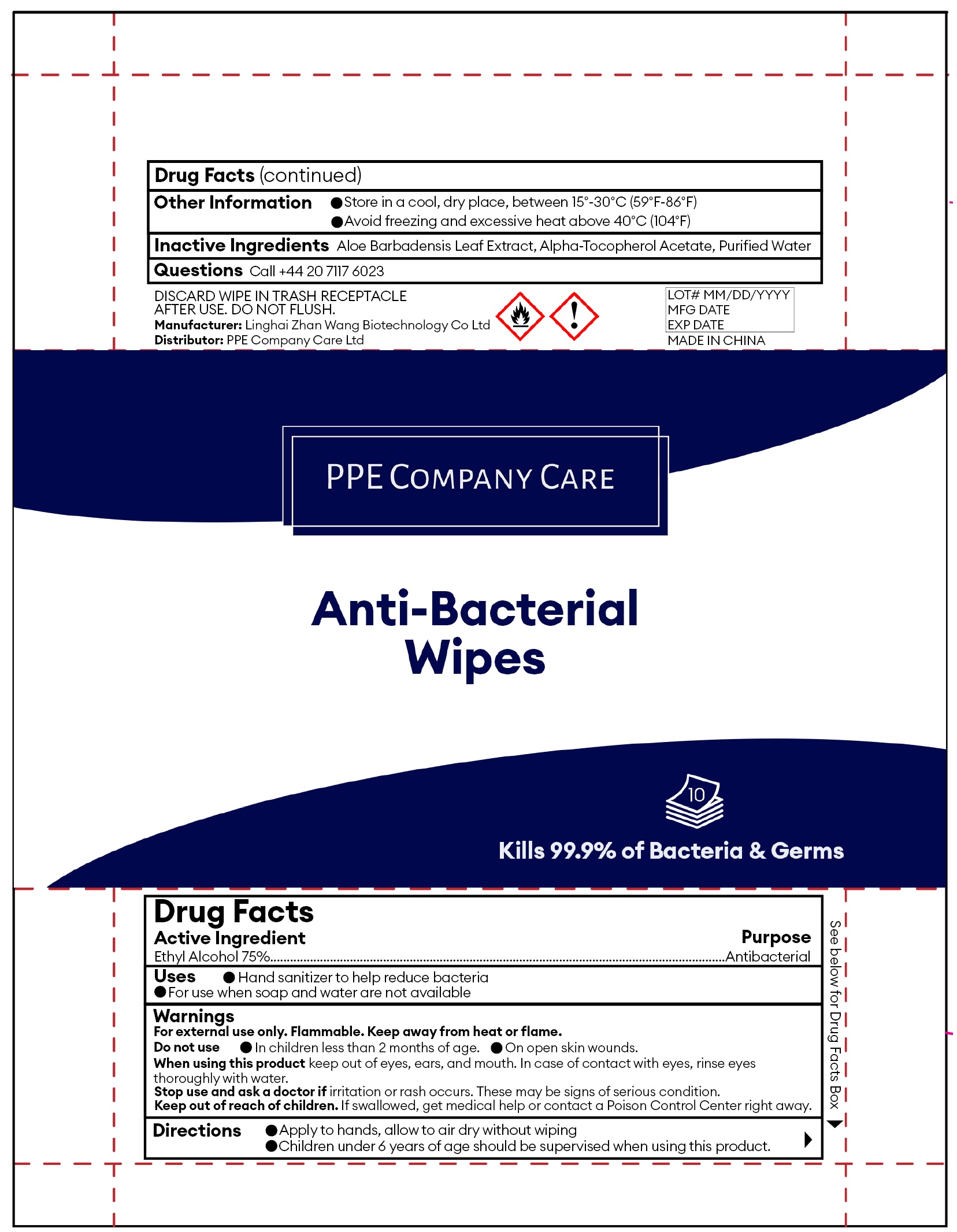 DRUG LABEL: PPE Company Care Antibacterial Wipes
NDC: 80856-002 | Form: CLOTH
Manufacturer: PPE Company Care Ltd
Category: otc | Type: HUMAN OTC DRUG LABEL
Date: 20201109

ACTIVE INGREDIENTS: ALCOHOL 0.75 mL/1 mL
INACTIVE INGREDIENTS: ALOE VERA LEAF; .ALPHA.-TOCOPHEROL ACETATE; WATER

PPE Company Care Antibacterial Wipes

Active Ingredient

Ethyl alcohol 75%

Purpose

Antibacterial

Uses

- Hand sanitiser to help reduce bacteria.
- For use when soap and water are not available.

Warnings

For external use only. Flammable. Keep away from heat or flame.

Do not use

- In children less than 2 months of age.
- On open skin wounds.

When using this product

keep out of eyes, ears, and mouth. In case of contact with eyes, rinse eyes thoroughly with water.

Stop use and ask a doctor

if irritation or rash occurs. These may be signs of a serious condition.

Keep out of reach of children.

If swallowed, get medical help or contact a Poison Control Centre right away.

Directions:

- Apply to hands, allow to air dry without wiping.
- Children under 6 years of age should be supervised when using this product.

Other Information

- Store in a cool, dry place, between 15°-30°C (59°F-86°F)
- Avoid freezing and excessive heat above 40°C (104°F)

Inactive Ingredients:

Aloe Barbadensis Leaf Extract, Alpha-Tocopherol Acetate, Purified Water

Questions

Call +44 20 7117 6023